DRUG LABEL: Unknown
Manufacturer: ImaRx Therapeutics, Inc.
Category: prescription | Type: HUMAN PRESCRIPTION DRUG LABELING
Date: 20070608

Kinlytic™
(urokinase for injection)

DESCRIPTION

Kinlytic™ (urokinase for injection) is a thrombolytic agent obtained from human neonatal kidney cells grown in tissue culture. The principal active ingredient of Kinlytic™ is the low molecular weight form of urokinase, and consists of an A chain of 2,000 daltons linked by a sulfhydryl bond to a B chain of 30,400 daltons. Kinlytic™ is supplied as a sterile lyophilized white powder containing 250,000 international units urokinase per vial, mannitol (25 mg/vial), Albumin (Human) (250 mg/vial), and sodium chloride (50 mg/vial).

Following reconstitution with 5 mL of Sterile Water for Injection, USP, Kinlytic™ is a clear, slightly straw-colored solution; each mL contains 50,000 international units of urokinase activity, 0.5% mannitol, 5% Albumin (Human), and 1% sodium chloride (pH range 6.0 to 7.5).

Thin translucent filaments may occasionally occur in reconstituted Kinlytic™ vials (see DOSAGE AND ADMINISTRATION).

Kinlytic™ is for intravenous infusion only.

Kinlytic™ is produced from human neonatal kidney cells (see WARNINGS). No fetal tissue is used in the production of Kinlytic™. Kidney donations are obtained exclusively in the United States from neonates (birth to 28 days) for whom death has not been attributed to infectious causes and that have exhibited no evidence of an infectious disease based in part, on an examination of the maternal and neonatal donor medical records. The maternal and neonatal donor screening process also identifies specific risk factors for known infectious diseases and includes testing of sera for HBV, HCV, HIV-1, HIV-2, HTLV-I, HTLV-II, CMV, and EBV. Donors with sera testing positive or associated with other risk factors are excluded. During the manufacturing process, cells are tested at multiple stages for the presence of viruses using in vitro and in vivo tests that are capable of detecting a wide range of viruses. Cells are also screened for HPV using a DNA detection-based test and for reovirus using a polymerase chain reaction-based test. The manufacturing process used for this product has been validated in laboratory studies to inactivate and/or remove a diverse panel of spiked model enveloped and non-enveloped viruses, and includes purification steps and a heat treatment step (10 hours at 60°C in 2% sodium chloride). A single vial of Kinlytic™ contains urokinase produced using cells derived from one or two donors.

CLINICAL PHARMACOLOGY

Urokinase is an enzyme (protein) produced by the kidney, and found in the urine. There are two forms of urokinase which differ in molecular weight but have similar clinical effects. Kinlytic™ is the low molecular weight form. Kinlytic™ acts on the endogenous fibrinolytic system. It converts plasminogen to the enzyme plasmin. Plasmin degrades fibrin clots as well as fibrinogen and some other plasma proteins.

Information about the pharmacokinetic properties in man is limited. Urokinase administered by intravenous infusion is rapidly cleared by the liver with an elimination half-life for biologic activity of 12.6 ± 6.2 minutes and a distribution volume of 11.5 L. Small fractions of the administered dose are excreted in bile and urine. Although the pharmacokinetics of exogenously administered urokinase have not been characterized in patients with hepatic impairment, endogenous urokinase-type plasminogen activator plasma levels are elevated 2- to 4-fold in patients with moderate to severe cirrhosis.^1 Thus, reduced urokinase clearance in patients with hepatic impairment might be expected.

Intravenous infusion of Kinlytic™ in doses recommended for lysis of pulmonary embolism is followed by increased fibrinolytic activity in the circulation. This effect disappears within a few hours after discontinuation, but a decrease in plasma levels of fibrinogen and plasminogen and an increase in the amount of circulating fibrin and fibrinogen degradation products may persist for 12-24 hours.^2 There is a lack of correlation between embolus resolution and changes in coagulation and fibrinolytic assay results.

Treatment with urokinase demonstrated more improvement on pulmonary angiography, lung perfusion scanning, and hemodynamic measurements within 24 hours than did treatment with heparin. Lung perfusion scanning showed no significant treatment-associated difference by day 7.^3

Information based on patients treated with fibrinolytics for pulmonary embolus suggests that improvement in angiographic and lung perfusion scans is lessened when treatment is instituted more than several days (e.g., 4 to 6 days) after onset.^4

INDICATIONS AND USAGE

Kinlytic™ is indicated in adults:

- For the lysis of acute massive pulmonary emboli, defined as obstruction of blood flow to a lobe or multiple segments.
- For the lysis of pulmonary emboli accompanied by unstable hemodynamics, i.e., failure to maintain blood pressure without supportive measures.

The diagnosis should be confirmed by objective means, such as pulmonary angiography or non-invasive procedures such as lung scanning.

CONTRAINDICATIONS

The use of Kinlytic™ is contraindicated in patients with a history of hypersensitivity to the product (see WARNINGS and ADVERSE REACTIONS).

Because thrombolytic therapy increases the risk of bleeding, Kinlytic™ is contraindicated in the situations listed below (see WARNINGS).

- Active internal bleeding
- Recent (e.g., within two months) cerebrovascular accident
- Recent (e.g., within two months) intracranial or intraspinal surgery
- Recent trauma including cardiopulmonary resuscitation
- Intracranial neoplasm, arteriovenous malformation, or aneurysm
- Known bleeding diatheses
- Severe uncontrolled arterial hypertension

WARNINGS

Bleeding

The risk of serious bleeding is increased with use of Kinlytic™. Fatalities due to hemorrhage, including intracranial and retroperitoneal, have been reported in association with urokinase therapy.

Concurrent administration of Kinlytic™ with other thrombolytic agents, anticoagulants, or agents inhibiting platelet function may further increase the risk of serious bleeding.

Kinlytic™ therapy requires careful attention to all potential bleeding sites (including catheter insertion sites, arterial and venous puncture sites, cutdown sites, and other needle puncture sites).

Intramuscular injections and nonessential handling of the patient must be avoided during treatment with Kinlytic™. Venipunctures should be performed as infrequently as possible and with care to minimize bleeding.

Should an arterial puncture be necessary, upper extremity vessels are preferable. Direct pressure should be applied for at least 30 minutes, a pressure dressing applied, and the puncture site checked frequently for evidence of bleeding.

In the following conditions, the risk of bleeding may be increased and should be weighed against the anticipated benefits:

- Recent (within 10 days) major surgery, obstetrical delivery, organ biopsy, previous puncture of non-compressible vessels
- Recent (within 10 days) serious gastrointestinal bleeding
- High likelihood of a left heart thrombus, for example, mitral stenosis with atrial fibrillation
- Subacute bacterial endocarditis
- Hemostatic defects including those secondary to severe hepatic or renal disease
- Pregnancy
- Cerebrovascular disease
- Diabetic hemorrhagic retinopathy
- Any other condition in which bleeding might constitute a significant hazard or be particularly difficult to manage because of its location

When internal bleeding occurs, it may be more difficult to manage than that which occurs with conventional anticoagulant therapy. Should potentially serious spontaneous bleeding (not controllable by direct pressure) occur, the infusion of Kinlytic™ should be terminated immediately, and measures to manage the bleeding implemented. Serious blood loss may be managed with volume replacement, including packed red blood cells. Dextran should not be used. When appropriate, fresh frozen plasma and/or cryoprecipitate may be considered to reverse the bleeding tendency.

Anaphylaxis and Other Infusion Reactions

Post-marketing reports of hypersensitivity reactions have included anaphylaxis (with rare reports of fatal anaphylaxis), bronchospasm, orolingual edema and urticaria (see ADVERSE REACTIONS: Allergic Reactions). There have also been reports of other infusion reactions which have included one or more of the following: fever and/or chills/rigors, hypoxia, cyanosis, dyspnea, tachycardia, hypotension, hypertension, acidosis, back pain, vomiting, and nausea. Reactions generally occurred within one hour of beginning Kinlytic™ infusion. Patients who exhibit reactions should be closely monitored and appropriate therapy instituted.

Infusion reactions generally respond to discontinuation of the infusion and/or administration of intravenous antihistamines, corticosteroids, or adrenergic agents.

Antipyretics which inhibit platelet function (aspirin and other non-steroidal anti-inflammatory agents) may increase the risk of bleeding and should not be used for treatment of fever.

Cholesterol Embolization

Cholesterol embolism has been reported rarely in patients treated with all types of thrombolytic agents; the true incidence is unknown. This serious condition, which can be lethal, is also associated with invasive vascular procedures (e.g., cardiac catheterization, angiography, vascular surgery) and/or anticoagulant therapy. Clinical features of cholesterol embolism may include livedo reticularis, “purple toe” syndrome, acute renal failure, gangrenous digits, hypertension, pancreatitis, myocardial infarction, cerebral infarction, spinal cord infarction, retinal artery occlusion, bowel infarction and rhabdomyolysis.

Product Source and Formulation with Albumin

Kinlytic™ is made from human neonatal kidney cells grown in tissue culture. Products made from human source material may contain infectious agents, such as viruses, that can cause disease. The risk that Kinlytic™ will transmit an infectious agent has been reduced by screening donors for prior exposure to certain viruses, by testing donors for the presence of certain current virus infections, by testing for certain viruses during manufacturing, and by inactivating and/or removing certain viruses during manufacturing (see DESCRIPTION). Despite these measures, Kinlytic™ may carry a risk of transmitting infectious agents, including those that cause Creutzfeldt-Jakob disease (CJD) or other diseases not yet known or identified; thus, the risk of transmission of infectious agents cannot be totally eliminated. A theoretical risk for transmission of Creutzfeldt-Jakob disease (CJD) is considered extremely remote.

This product is formulated in 5% albumin, a derivative of human blood. Based on effective donor screening and product manufacturing processes, albumin carries an extremely remote risk for transmission of viral diseases. A theoretical risk for transmission of Creutzfeldt-Jakob disease (CJD) also is considered extremely remote. No cases of transmission of viral diseases or CJD have ever been identified for albumin.

All infections thought by a physician possibly to have been transmitted by this product should be reported by the physician or other healthcare provider to ImaRx Therapeutics, Inc. [1-866-634-6279].

PRECAUTIONS

General

Kinlytic™ should be used in hospitals where the recommended diagnostic and monitoring techniques are available.

The clinical response and vital signs should be observed frequently during and following Kinlytic™ infusion. Blood pressure should not be taken in the lower extremities to avoid dislodgement of possible deep vein thrombi.

Laboratory Tests

Before beginning thrombolytic therapy, obtain a hematocrit, platelet count, and an activated partial thromboplastin time (aPTT). If heparin has been given, it should be discontinued and the aPTT should be less than twice the normal control value before thrombolytic therapy is started.

Following intravenous infusion of Kinlytic™, before (re)instituting anticoagulants, the aPTT should be less than twice the normal control value.

Results of coagulation tests and measures of fibrinolytic activity do not reliably predict either efficacy or risk of bleeding for patients receiving Kinlytic™.

Drug Interactions

Anticoagulants and agents that alter platelet function (such as aspirin, other non-steroidal anti-inflammatory agents, dipyridamole, and GP IIb/IIIa inhibitors) may increase the risk of serious bleeding.

Administration of Kinlytic™ prior to, during, or after thrombolytic agents may increase the risk of serious bleeding.

Because concomitant use of Kinlytic™ with agents that alter coagulation, inhibit platelet function, or are thrombolytic may further increase the potential for bleeding complications, careful monitoring for bleeding is recommended.

The interaction of Kinlytic™ with other drugs has not been studied and is not known.

Carcinogenicity

Adequate data are not available on the long-term potential for carcinogenicity in animals or humans.

Pregnancy

Pregnancy Category B: Reproduction studies have been performed in mice and rats at doses up to 1,000 times the human dose and have revealed no evidence of impaired fertility or harm to the fetus due to Kinlytic™. There are, however, no adequate and well-controlled studies in pregnant women. Because animal reproduction studies are not always predictive of human response, this drug should be used during pregnancy only if clearly needed.

Nursing Mothers

It is not known whether this drug is excreted in human milk. Because many drugs are excreted in human milk, caution should be exercised when Kinlytic™ is administered to a nursing woman.

Pediatric Use

Safety and effectiveness in pediatric patients have not been established.

Geriatric Use

Clinical studies of Kinlytic™ did not include sufficient numbers of subjects aged 65 and over to determine whether they respond differently from younger subjects. Kinlytic™ should be used with caution in elderly patients.

ADVERSE REACTIONS

The most serious adverse reactions reported with Kinlytic™ administration include fatal hemorrhage and anaphylaxis (see WARNINGS).

Bleeding

Bleeding is the most frequent adverse reaction associated with Kinlytic™ and can be fatal (see WARNINGS).

In controlled clinical studies using a 12-hour infusion of urokinase for the treatment of pulmonary embolism (UPET and USPET),^3,5,6 bleeding resulting in at least a 5% decrease in hematocrit was reported in 52 of 141 urokinase-treated patients. Significant bleeding events requiring transfusion of greater than 2 units of blood were observed during the 14-day study period in 3 of 141 urokinase-treated patients in these studies. Multiple bleeding events may have occurred in an individual patient. Most bleeding occurred at sites of external incisions and vascular puncture, with lesser frequency in gastrointestinal, genitourinary, intracranial, retroperitoneal, and intramuscular sites.

Sources of Information on Adverse Reactions

There are limited well-controlled clinical studies performed using urokinase. The adverse reactions described in the following sections reflect both the clinical use of Kinlytic™ in the general population and limited controlled study data. Because post-marketing reports of adverse reactions are voluntary and the population is of uncertain size, it is not always possible to reliably estimate the frequency of the reaction or establish a causal relationship to drug exposure.

Allergic Reactions

Rare cases of fatal anaphylaxis have been reported (see WARNINGS). In controlled clinical trials, allergic reaction was reported in 1 of 141 patients (<1%).

The following allergic-type reactions have been observed in clinical trials and/or post-marketing experience: bronchospasm, orolingual edema, urticaria, skin rash, and pruritus (see WARNINGS).

Infusion reaction symptoms include hypoxia, cyanosis, dyspnea, tachycardia, hypotension, hypertension, acidosis, fever and/or chills/rigors, back pain, vomiting, and nausea (see WARNINGS).

Other Adverse Reactions

Other adverse events occurring in patients receiving Kinlytic™ therapy in clinical studies, regardless of causality, include myocardial infarction, recurrent pulmonary embolism, hemiplegia, stroke, decreased hematocrit, substernal pain, thrombocytopenia, and diaphoresis.

Additional adverse reactions reported from post-marketing experience include cardiac arrest, vascular embolization (cerebral and distal) including cholesterol emboli (see WARNINGS), cerebral vascular accident, pulmonary edema, reperfusion ventricular arrhythmias and chest pain. A cause and effect relationship has not been established.

Immunogenicity

The immunogenicity of Kinlytic™ has not been studied.

DOSAGE AND ADMINISTRATION

Kinlytic™ IS INTENDED FOR INTRAVENOUS INFUSION ONLY.

Kinlytic™ treatment should be instituted soon after onset of pulmonary embolism. Delay in instituting therapy may decrease the potential for optimal efficacy (see CLINICAL PHARMACOLOGY).

Dosing

- A loading dose of 4,400 international units per kilogram of Kinlytic™ is given at a rate of 90 mL per hour over a period of 10 minutes. This is followed by a continuous infusion of 4,400 international units per kilogram per hour at a rate of 15 mL for 12 hours.
- Administration of Kinlytic™ may be repeated as necessary.
- A dosing and preparation chart for patients who weigh 37 to 114 kilograms (81 to 250 pounds) is provided as a guide in the Preparation Section that follows below. If the patient is outside of these weights, calculate with dosing information provided above.

Preparation

- The Dose Preparation-Pulmonary Embolism chart is a guidance tool/aid provided for the convenience of the practitioner and may not be complete for every patient.
- Kinlytic™ contains no preservatives. Do not reconstitute until immediately before use. Any unused portion of the reconstituted material should be discarded.
- Reconstitute Kinlytic™ by aseptically adding 5 mL of Sterile Water for Injection, USP, without preservatives, to the vial. DO NOT USE Bacteriostatic Water for Injection, USP.
- After reconstitution, the drug product will contain 50,000 international units per milliliter.
- After reconstituting, visually inspect each vial of Kinlytic™ for discoloration and for the presence of particulate material. The solution should be pale and straw-colored; highly colored solutions should not be used. Thin translucent filaments may occasionally occur in reconstituted Kinlytic™ vials, but do not indicate any decrease in potency of this product. To minimize formation of filaments, avoid shaking the vial during reconstitution. Roll and tilt the vial to enhance reconstitution. The solution may be terminally filtered, for example, through a 0.45 micron or smaller cellulose membrane filter.
- No other medication should be added to this solution.
- Prior to infusing, dilute the reconstituted Kinlytic™ with 0.9% Sodium Chloride Injection, USP or 5% Dextrose Injection, USP.

The following Dose Preparation-Pulmonary Embolism chart may be used as an aid in the preparation of Kinlytic™ for administration. For administration directions, see next section.

Dose Preparation-Pulmonary Embolism
Patient Weight [kilograms (pounds)] | Total Dosea (Loading and Continuous Infusion) | Number of Kinlytic™ Vials Needed for Total Dose | Total Volume of Sterile Water for Injection needed for Reconstitution of Kinlytic™ Vialsb | + | Volume of 0.9% Sodium Chloride or 5% Dextrose Injection, USP for Infusion (mL) | = | Final Volume (mL) for Loading and Continuous Infusion
37-40 (81-90) | 2,250,000 | 9 | 45 |  | 150 |  | 195
41-45 (91-100) | 2,500,000 | 10 | 50 |  | 145 |  | 195
46-50 (101-110) | 2,750,000 | 11 | 55 |  | 140 |  | 195
51-54(111-120) | 3,000,000 | 12 | 60 |  | 135 |  | 195
55-59(121-130) | 3,250,000 | 13 | 65 |  | 130 |  | 195
60-64 (131-140) | 3,500,000 | 14 | 70 |  | 125 |  | 195
65-68(141-150) | 3,750,000 | 15 | 75 |  | 120 |  | 195
69-73 (151-160) | 4,000,000 | 16 | 80 |  | 115 |  | 195
74-77 (161-170) | 4,250,000 | 17 | 85 |  | 110 |  | 195
78-82 (171-180) | 4,500,000 | 18 | 90 |  | 105 |  | 195
83-86 (181-190) | 4,750,000 | 19 | 95 |  | 100 |  | 195
87-91 (191-200) | 5,000,000 | 20 | 100 |  | 95 |  | 195
92-95 (201-210) | 5,250,000 | 21 | 105 |  | 90 |  | 195
96-100 (211-220) | 5,500,000 | 22 | 110 |  | 85 |  | 195
101-104 (221-230) | 5,750,000 | 23 | 115 |  | 80 |  | 195
105-109 (231-240) | 6,000,000 | 24 | 120 |  | 75 |  | 195
110-114 (241-250) | 6,250,000 | 25 | 125 |  | 70 |  | 195
a Loading Dose + dose administered during 12-hour period.
b Each vial is reconstituted with 5 mL of Sterile Water for Injection, USP, without preservatives. (See Preparation.)

Administration

- Kinlytic™ is administered using a constant infusion pump that is capable of delivering a total volume of 195 mL.
- The loading dose of Kinlytic™ admixture (4,400 international units per kilogram) should be delivered at a rate of 90 mL per hour over a period of 10 minutes.
- This is followed by a continuous infusion of 4,400 international units per kilogram per hour of Kinlytic™ at a rate of 15 mL per hour for 12 hours.
- Since some of the Kinlytic™ admixture will remain in the tubing at the end of an infusion pump delivery cycle, the following flush procedure should be performed to insure that the total dose of Kinlytic™ is administered. A solution of 0.9% Sodium Chloride Injection, USP, or 5% Dextrose Injection, USP, approximately equal in amount to the volume of the tubing in the infusion set should be administered via the pump to flush the Kinlytic™ admixture from the entire length of the infusion set. The pump should be set to administer the flush solution at the continuous rate of 15 mL per hour.
- No other drug products/solutions may be administered in the same line with Kinlytic™.

Anticoagulation After Terminating Kinlytic™ Treatment

After infusing Kinlytic™, anticoagulation treatment is recommended to prevent recurrent thrombosis. Do not begin anticoagulation until the aPTT has decreased to less than twice the normal control value. If heparin is used, do not administer a loading dose of heparin. Treatment should be followed by oral anticoagulants.

HOW SUPPLIED

Kinlytic™ is supplied as a sterile lyophilized preparation (NDC 24430-1003-1). Each vial contains 250,000 international units urokinase activity, 25 mg mannitol, 250 mg Albumin (Human), and 50 mg sodium chloride. Refrigerate Kinlytic™ powder at 2° to 8°C (36° to 46°F) (See USP).

REFERENCES

1. Sato S. et al. Elevated Urokinase-Type Plasminogen Activator Plasma Levels Are Associated With Deterioration of Liver Function But Not With Hepatocellular Carcinoma. J Gastroenterology, 1994; 29:745-750.
2. Bell WR. Thrombolytic Therapy: A Comparison Between Urokinase and Streptokinase. Sem Thromb Hemost. 1975; 2:1-13.
3. Sasahara AA, Hyers TM, Cole CM, et al. The Urokinase Pulmonary Embolism Trial. Circulation. 1973; 47 (suppl. 2):1-108.
4. Daniels LB, Parker JA, Patel SR, Grodstein F, Goldhaber SZ. Relation of Duration of Symptoms With Response to Thrombolytic Therapy in Pulmonary Embolism. Am J Cardiol. 1997; 80:184-188.
5. Urokinase Pulmonary Embolism Trial Study Group: Urokinase-Streptokinase Embolism Trial. JAMA. 1974; 229:1606-1613.
6. Sasahara AA, Bell WR, Simon TL, et al. The Phase II Urokinase-Streptokinase Pulmonary Embolism Trial. Thrombos Diathes Haemorrh (Stuttg). 1975; 33:464-476.

Rx

©ImaRx Therapeutics, Inc. 2007

Printed in USA

ImaRx Therapeutics, Inc. Tucson Arizona, 85719, USA

Ref: 80003 V:01 June 2007